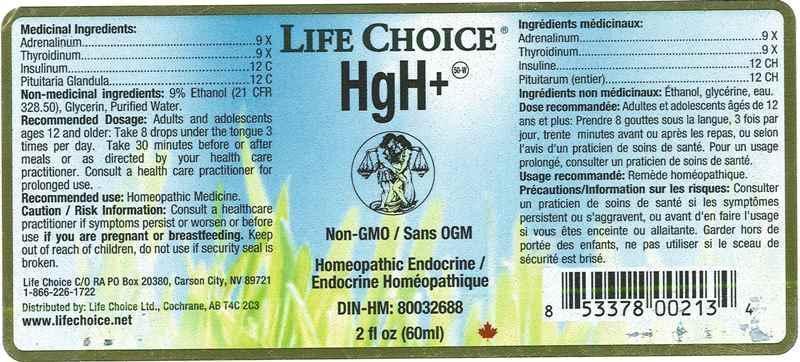 DRUG LABEL: HGH
NDC: 55856-0001 | Form: LIQUID
Manufacturer: Life Choice Ltd.
Category: homeopathic | Type: HUMAN OTC DRUG LABEL
Date: 20150109

ACTIVE INGREDIENTS: EPINEPHRINE 9 [hp_X]/1 mL; SUS SCROFA THYROID 9 [hp_X]/1 mL; INSULIN PORK 12 [hp_C]/1 mL; SUS SCROFA PITUITARY GLAND 12 [hp_C]/1 mL
INACTIVE INGREDIENTS: WATER; GLYCERIN; ALCOHOL

DRUG FACTS:

ACTIVE INGREDIENTS:

ADRENALINUM 9X, THYROIDINUM (SUIS) 9X, INSULINUM 12C, PITUITARIA GLANDULA (SUIS) 12C

RECOMMENDED USE:

Homeopathic medicine.

CAUTION/RISK INFORMATION:

Consult a healthcare practitioner if symptoms persist or worsen or before use if you are pregnant or breastfeeding.

Keep out of reach of children, do not use if security seal is broken.

KEEP OUT OF REACH OF CHILDREN:

RECOMMENDED DOSAGE:

Adults and adolescents ages 12 and older: Take 8 drops under the tongue 3 times per day. Take 30 minutes before or after meals or as directed by your health practitioner. Consult a health care practitioner for prolonged use.

RECOMMENDED USE:

Homeopathic medicine.

NON-MEDICINAL INGREDIENTS:

9% Ethanol (21 CFR 328.50), Glycerin, Purified Water.

QUESTIONS:

Life Choice C/O RA

PO Box 20380, Carson City, NV 89721

1-866-226-1722

Distributed by: Life Choice Ltd., Cochrane AB T4C 2C3

www.lifechoice.net

PACKAGE LABEL DISPLAY:

LIFE CHOICE

HgH+

Non-GMO / Sans OGM

Homeopathic Endocrine /

Endocrine Homéopathique

DIN-HM: 80032688

2 fl oz (60ml)